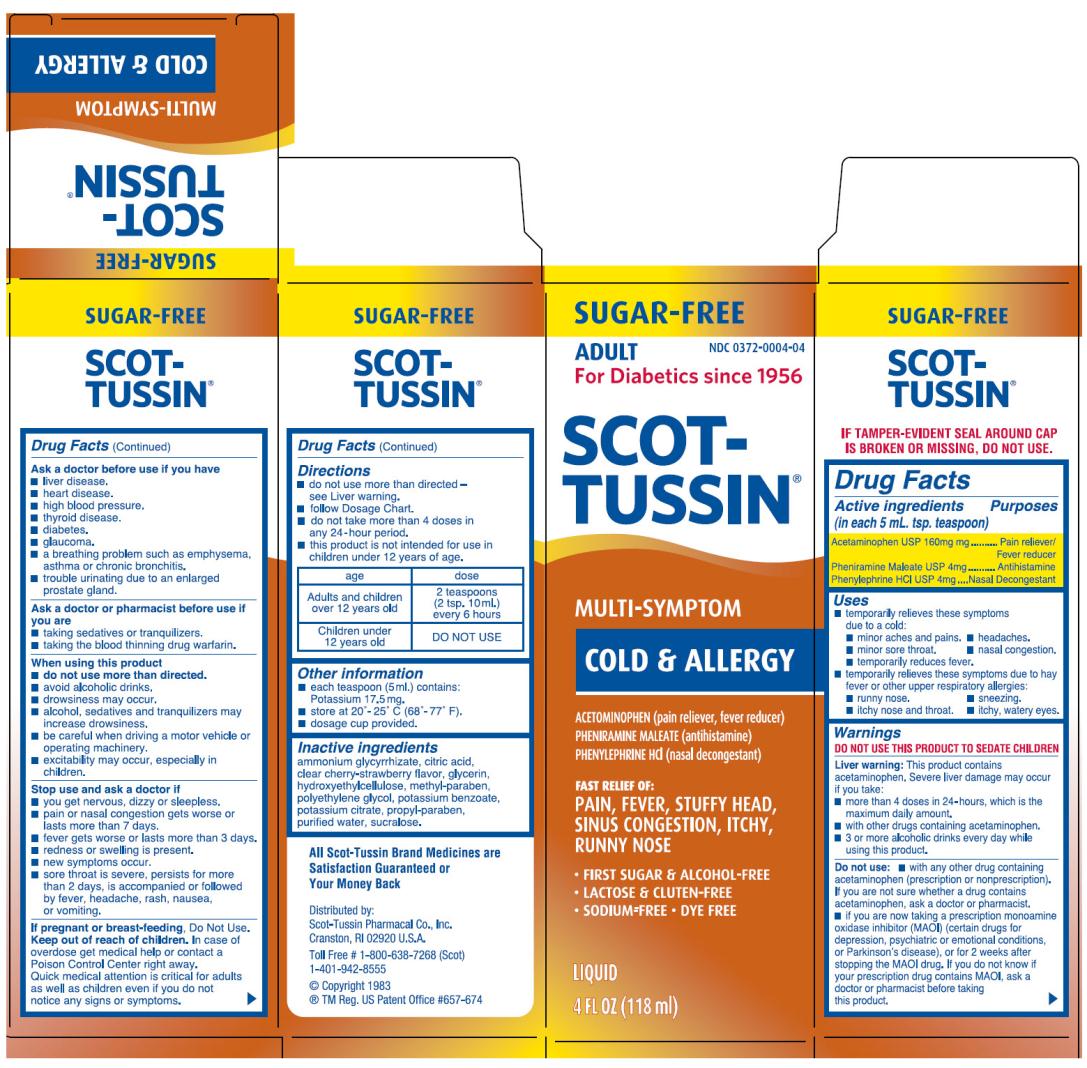 DRUG LABEL: Scot-Tussin Original SF Multi-Symptom
NDC: 0372-0004 | Form: LIQUID
Manufacturer: SCOT-TUSSIN Pharmacal Co., Inc.
Category: otc | Type: HUMAN OTC DRUG LABEL
Date: 20130125

ACTIVE INGREDIENTS: ACETAMINOPHEN 160 mg/5 mL; PHENYLEPHRINE HYDROCHLORIDE 4 mg/5 mL; PHENIRAMINE MALEATE 4 mg/5 mL
INACTIVE INGREDIENTS: AMMONIUM GLYCYRRHIZATE; CITRIC ACID MONOHYDRATE; GLYCERIN; HYDROXYETHYL CELLULOSE (2000 MPA.S AT 1%); METHYLPARABEN; POLYETHYLENE GLYCOLS; POTASSIUM BENZOATE; POTASSIUM CITRATE; PROPYLPARABEN; SUCRALOSE; WATER

Scot-Tussin Original SF Multi-Symptom

Active Ingredient

(in each 5 mL. tsp. teaspoon)
Acetaminophen USP 160 mg

Purpose

Pain reliever/Fever reducer

Active Ingredient

(in each 5 mL. tsp. teaspoon)
Pheniramine Maleate USP 4 mg

Purpose

Antihistamine

Active Ingredient

(in each 5 mL. tsp. teaspoon)
Phenylephrine HCI USP 4 mg

Purpose

Decongestant

Uses

- temporarily relieves these symptoms due to a cold:
  - minor aches and pains.
  - minor sore throat.
  - temporarily reduces fever.
  - headaches.
  - nasal congestion.
- temporarily relieves these symptoms due to hay fever or other upper respiratory allergies:
  - runny nose.
  - itchy nose and throat.
  - sneezing.
  - itchy, watery eyes.

Warnings

DO NOT USE THIS PRODUCT TO SEDATE CHILDREN

Liver warning: This product contains acetaminophne. Severe liver damange may occur if you take:

- more than 4 doses in 24-hours, which is the maximum daily amount.
- with other drugs containing acetaminophen.
- 3 or more alcoholic drinks every day while using this product.

Do not use

- with any other drug containing acetaminophen (prescription or nonprescription). If you are not sure whether a drug contains acetaminophen, ask a doctor or pharmacist.
- if you are now taking a prescription monoamie oxidase inhibitor (MAOI) (certain drugs for depression, psychiatric or emotional conditions, or Parkinson's disease), or for 2 weeks after stopping the MAOI drug. If you do not know if your prescription drug contains MAOI, ask a doctor or pharmacist before taking this product.

Ask a doctor before use if you have

- liver disease.
- heart disease.
- high blood pressure.
- thyroid disease.
- diabetes.
- glaucoma.
- a breathing problem such as emphysema, asthma or chronic broncititis.
- trouble uritinating due to an enlarged prostate gland.

Ask a doctor or pharmacist before use if you are

- taking sedatives or tranquilizers.
- taking the blood thinning drug warfarin.

When using this product

- do not use more than directed.
- avoid alcoholic drinks.
- drowsiness may occur.
- alcohol, sedatives and tranquilizers may increase drowsiness.
- be careful when driving a motor vehicle or operating machinery.
- excitability may occur, especially in children.

Stop use and ask a doctor if

- you get nervous, dizzy or sleepless.
- pain or nasal congestion gets worse or lasts more than 7 days.
- fever gets worse or lasts more than 3 days.
- redness or swelling is present.
- new symptoms occur.
- sore throat is severe, persists for more than 2 days, is accompanied or followed by fever, headache, rash, nausea, or vomiting.

If pregnant or breast-feeding,

Do Not Use

Keep out of reach of children.

In case of overdose get medical help or contact a Poison Control Center right away. Quick medical attention is critical for adults as well as children even if you do not notice any signs or symptoms.

Directions

- do not use more than directed - see Liver warning.
- follow Dosage Chart.
- do not take more than 4 doses in any 24-hour period.
- this product is not intended for use in children under 12 years of age.

age | dose
Adults and children over 12 years old | 2 teaspoons (2 tsp. 10ml.) every 6 hours
Children under 12 years old | DO NOT USE

Other Information

- each teaspoon (5 ml.) contains:
  Potassium 17.5 mg.
- Store at 20º – 25º C (68º – 77º F).
- do not refrigerate.
- dosage cup provided.

Inactive Ingredients

ammonium glycyrrhizate, citric acid, clear cherry-strawberry flavor, glycerin, hydroxyethylcellulose, methyl paraben, polyethylene glycol, potassium benzoate, potassium citrate, propyl paraben, purified water, sucralose.

PRINCIPAL DISPLAY PANEL

SCOT-
TUSSIN
MULTI-SYMPTOM
COLD & ALLERGY